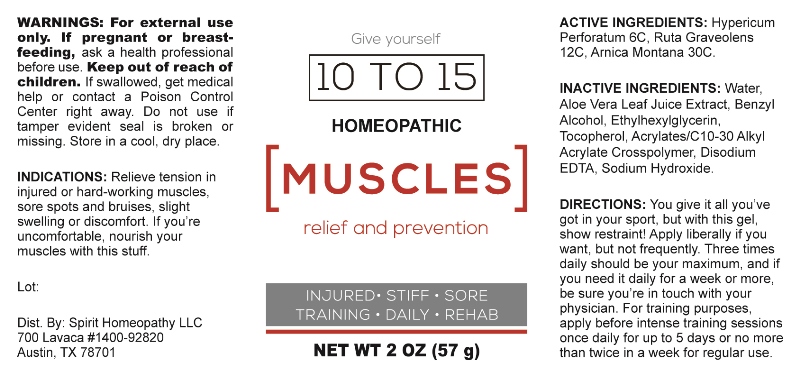 DRUG LABEL: Muscles
NDC: 73300-0001 | Form: GEL
Manufacturer: Spirit Homeopathy LLC
Category: homeopathic | Type: HUMAN OTC DRUG LABEL
Date: 20240122

ACTIVE INGREDIENTS: HYPERICUM PERFORATUM 6 [hp_C]/1 mL; RUTA GRAVEOLENS FLOWERING TOP 12 [hp_C]/1 mL; ARNICA MONTANA 30 [hp_C]/1 mL
INACTIVE INGREDIENTS: WATER; CARBOMER INTERPOLYMER TYPE A (ALLYL SUCROSE CROSSLINKED); BENZYL ALCOHOL; ETHYLHEXYLGLYCERIN; TOCOPHEROL; SODIUM HYDROXIDE; ALOE VERA LEAF; EDETATE DISODIUM

Drug Facts:

ACTIVE INGREDIENTS:

Hypericum Perforatum 6C, Ruta Graveolens 12C, Arnica Montana 30C.

INDICATIONS:

Relieve tension in injured or hard-working muscles, sore spots and bruises, slight swelling or discomfort. If you're uncomfortable, nourish your muscles with this stuff.

WARNINGS:

For external use only. If pregnant or breast-feeding, ask a health professional before use.

Keep out of reach of children. If swallowed, get medical help or a Poison Control Center right away.

Store in a cool, dry place.

Keep out of reach of children. In case of overdose, contact physician or a Poison Control Center right away.

DIRECTIONS:

1-10 drops under the tongue, 3 times a day or as directed by a health professional. Consult a physician for use in children under 12 years of age.

INDICATIONS:

Relieve tension in injured or hard-working muscles, sore spots and bruises, slight swelling or discomfort. If you're uncomfortable, nourish your muscles with this stuff.

INACTIVE INGREDIENTS:

Water, Aloe Vera Leaf Juice Extract, Benzyl Alcohol, Ethylhexylglycerin, Tocopherol, Acrylates/C/10-30 Alkyl Acrylate Crosspolymer, Disodium EDTA, Sodium Hydroxide.

QUESTIONS:

Dist. By: Spirit Homeopathy LLC

700 Lavaca #1400-92820

Austin, TX 78701

PACKAGE LABEL DISPLAY:

Give yourself

10 TO 15

HOMEOPATHIC

[MUSCLES]

relief and prevention

INJURED • STIFF • SORE

TRAINING • DAILY • REHAB

NET WT 2 OZ (57 g)